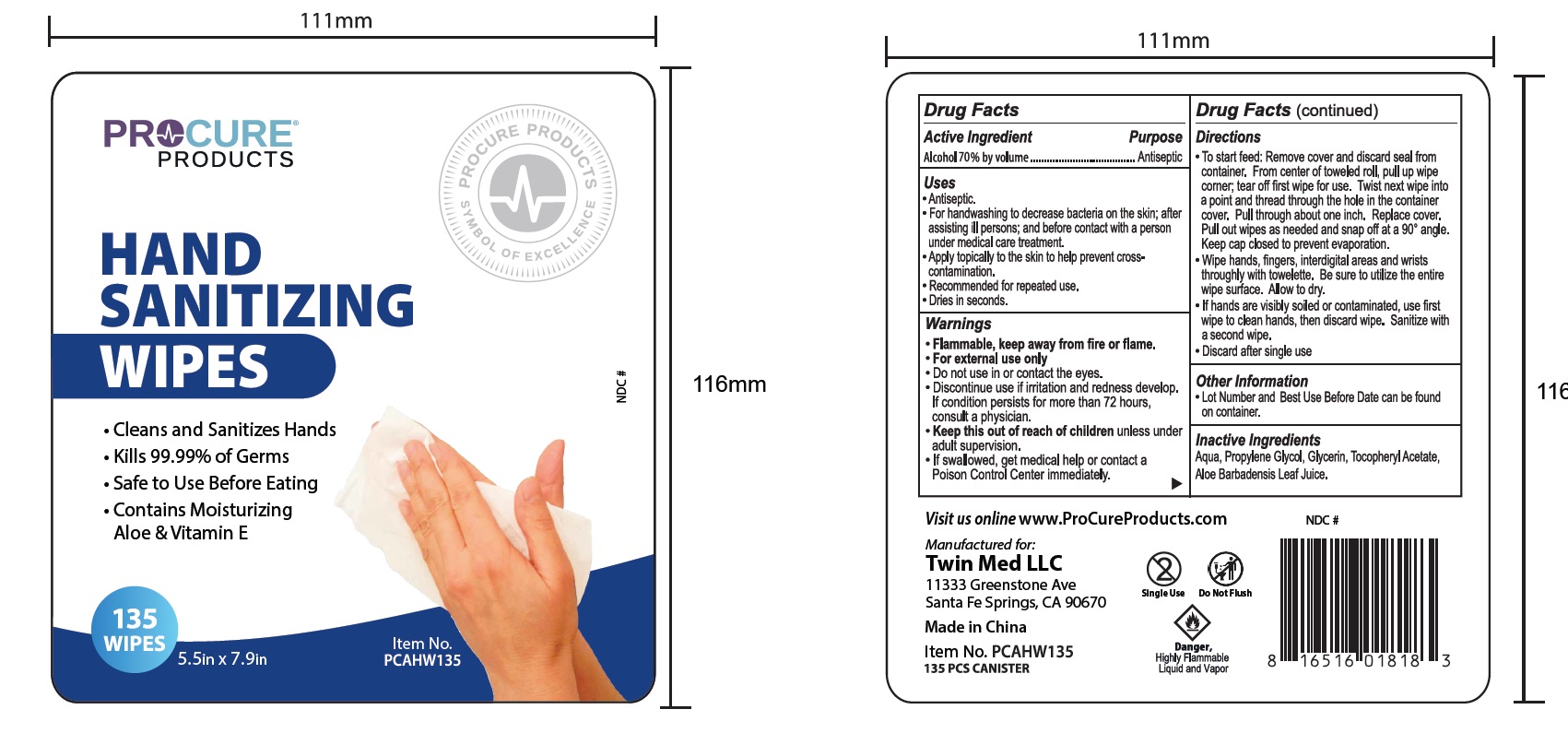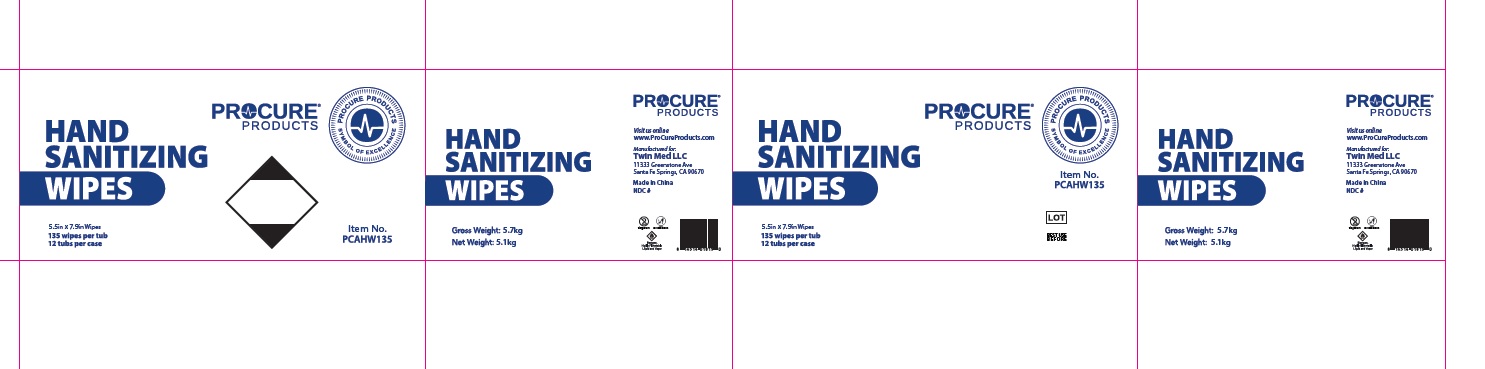 DRUG LABEL: Procure Products Hand Sanitizing Wipes
NDC: 55681-135 | Form: PATCH
Manufacturer: TWIN MED LLC
Category: otc | Type: HUMAN OTC DRUG LABEL
Date: 20250228

ACTIVE INGREDIENTS: ALCOHOL 70 mL/100 mL
INACTIVE INGREDIENTS: PROPYLENE GLYCOL; GLYCERIN; WATER; .ALPHA.-TOCOPHEROL ACETATE; ALOE VERA LEAF

Procure Hand Sanitizing Wipes

Active Ingredient

Alcohol 70% by Volume

Purpose

Antiseptic

Uses

- Antiseptic
- For handwashing to decrease bacteria on the skin, after assisting ill persons, and before contact with a person under medical care treatment
- Apply topically to the skin to help prevent cross contamination
- Recommended for repeated use
- Dries in seconds

Warnings

- Flammable, keep away from fire or flame'
- For external use only

Do not use

in or contact the eyes

Discontinue use if

irritation and redness develops. If condition persists for more than 72 hours, cosult a physician.

Keep this out of reach of children

unless under adult supervision. If swallowed, get medical help or contact a Poison Control Center immediately.

Directions

- To start feed: Remove Cover and discard seal from container. From center of toweled roll, pull up wipe corner, tear of first wipe for use. Twist next wipe into a point and thread through the hole in the container cover. Pull through about one inch. Replace cover. Pull wipes as needed and snap off at a 90° angle. Keep cap closed to prevent evaporation.
  - Wipe hands, fingers, interdigital areas and wrists throughly with towelette, Be sure to utilize the entire wipe surface. Allow to dry.
    - If hands are visibly soiled or contaminated, use first wipe to clean hands then discard wipe. Sanitize with a second wipe.
    - Discard after single use.

Other information

Lot Number and Best Use Before Date can be found on container

Inactive ingredients

Aqua, Propylene Glycol, Glycerin, Tocopheryl Acetate, Aloe Barbadensis Leaf Juice.

Principal Display Panel

NDC: 55681-135-02